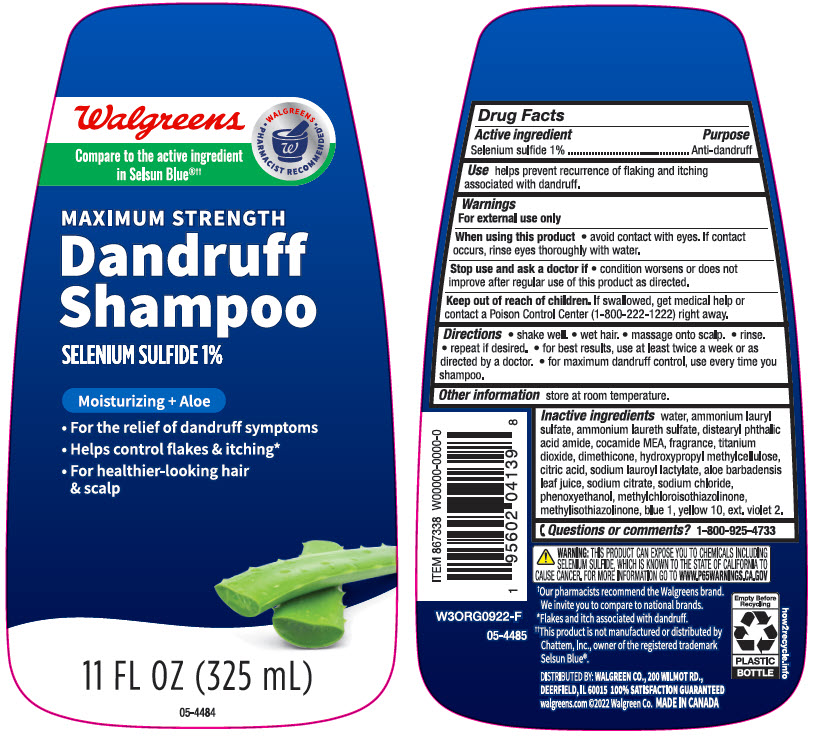 DRUG LABEL: Walgreens Dandruff Maximum Strength
NDC: 0363-4139 | Form: SHAMPOO
Manufacturer: Walgreen Company
Category: otc | Type: HUMAN OTC DRUG LABEL
Date: 20241101

ACTIVE INGREDIENTS: Selenium Sulfide 10 mg/1 mL
INACTIVE INGREDIENTS: Water; Ammonium Lauryl Sulfate; DISTEARYL PHTHALAMIC ACID; COCO MONOETHANOLAMIDE; Glycerin; Titanium Dioxide; Dimethicone; HYPROMELLOSE, UNSPECIFIED; CITRIC ACID MONOHYDRATE; SODIUM LAUROYL LACTYLATE; SODIUM CITRATE, UNSPECIFIED FORM; Sodium Chloride; Phenoxyethanol; Methylchloroisothiazolinone; Methylisothiazolinone; FD&C BLUE NO. 1; D&C YELLOW NO. 10; EXT. D&C VIOLET NO. 2

Walgreens Dandruff Shampoo Maximum Strength
Anti-dandruff

Drug Facts

Active ingredient

Selenium Sulfide 1%

Purpose

Anti-dandruff

Use

helps prevent recurrence of flaking and itching associated with dandruff.

Warnings

For external use only

When using this product

- avoid contact with the eyes. If contact occurs, rinse eyes thoroughly with water.

Stop use and ask a doctor if

- condition worsens or does not improve after regular use as directed.

Keep out of reach of children. If swallowed, get medical help or contact a Poison Control Center (1-800-222-1222) right away.

Directions

- shake well
- wet hair
- massage onto scalp
- rinse
- repeat if desired
- for best results use at least twice a week or as directed by a doctor
- for maximum dandruff control, use every time you shampoo.

Other information

store at room temperature

Inactive ingredients

water, ammonium lauryl sulfate, ammonium laureth sulfate, distearyl phthalic acid amide, cocamide MEA, fragrance, titanium dioxide, dimethicone, hydroxypropyl methylcellulose, citric acid, sodium lauroyl lactylate, aloe barbadensis leaf juice, sodium citrate, sodium chloride, phenoxyethanol, methylchloroisothiazolinone, methylisothiazolinone, blue 1, yellow 10, ext. violet 2.

Questions or Comments?

1-800-925-4733

DISTRIBUTED BY: WALGREEN CO. 200 WILMOT RD.,
DEERFIELD, IL 60015

PRINCIPAL DISPLAY PANEL - 325 mL Bottle Label

Walgreens

• WALGREENS •
PHARMACIST RECOMMENDED†

Compare to the active ingredient
in Selsun Blue®††

MAXIMUM STRENGTH

Dandruff
Shampoo

SELENIUM SULFIDE 1%

Moisturizing + Aloe

- For the relief of dandruff symptoms
- Helps control flakes & itching*
- For healthier-looking hair
  & scalp

11 FL OZ (325 mL)

05-4484